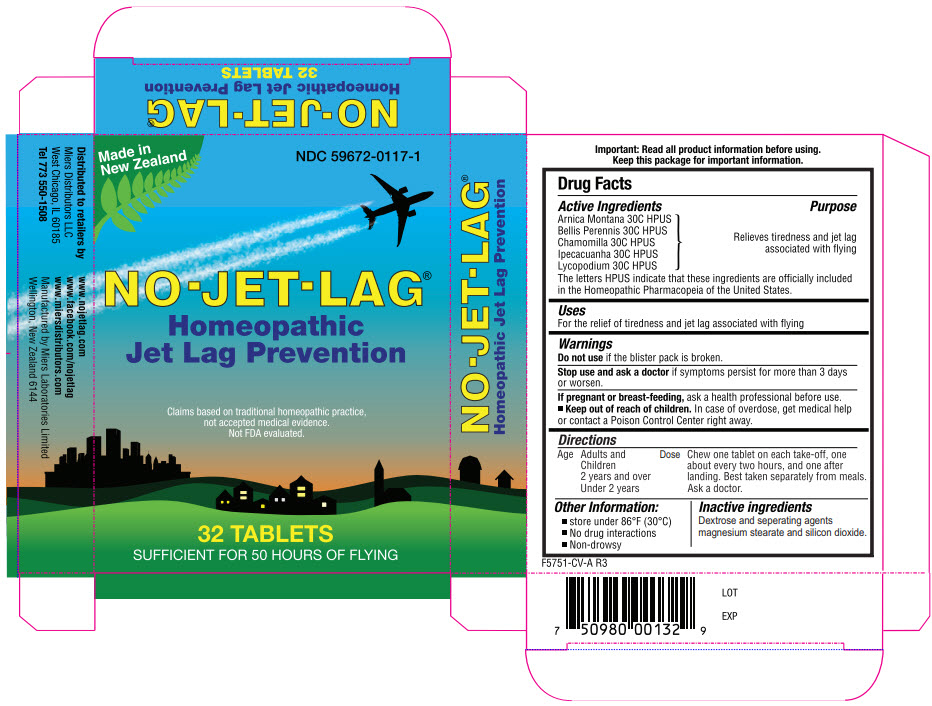 DRUG LABEL: NO-JET-LAG
NDC: 59672-0117 | Form: TABLET
Manufacturer: Miers Laboratories
Category: homeopathic | Type: HUMAN OTC DRUG LABEL
Date: 20240507

ACTIVE INGREDIENTS: ARNICA MONTANA WHOLE 30 [hp_C]/1 1; BELLIS PERENNIS WHOLE 30 [hp_C]/1 1; MATRICARIA CHAMOMILLA WHOLE 30 [hp_C]/1 1; IPECAC 30 [hp_C]/1 1; LYCOPODIUM CLAVATUM SPORE 30 [hp_C]/1 1
INACTIVE INGREDIENTS: DEXTROSE, UNSPECIFIED FORM 250 mg/1 1; Silicon Dioxide; Magnesium stearate

NO-JET-LAG® 16 tab

Drug Facts

Active Ingredients

Arnica Montana 30C HPUS
Bellis Perennis 30C HPUS
Chamomilla 30C HPUS
Ipecacuanha 30C HPUS
Lycopodium 30C HPUS

Purpose

To reduce jet lag

The letters HPUS indicate that these ingredients are officially included in the Homeopathic Pharmacopeia of the United States.

Uses

For the relief of tiredness and jet lag associated with flying

Warnings

Do not use if the blister pack is broken.

Ask a doctor before use in children under 2 years of age.

Stop use and ask a doctor if symptoms persist for more than 3 days or worsen.

PREGNANCY OR BREAST FEEDING

If pregnant or breast-feeding, ask a health professional before use.

Keep out of reach of children.

Directions

Age | Dose
Adults and Children 2 years and over | Chew one tablet on each take-off, one about every two hours, and one after landing. However, intervals of up to four hours between tablets are acceptable if sleeping. Best taken separately from meals.
Under 2 yrs | Ask a doctor.

Other Information

- store under 86°F (30°C)
- No drug interactions
- Non-drowsy

Inactive ingredients

Dextrose, and separating agents magnesium stearate and silicon dioxide.

Distributed by
LC Industries Inc, Elk Grove Village
IL 60007

PRINCIPAL DISPLAY PANEL - 32 Tablet Blister Pack Carton

Made in
New Zealand

NDC 59672-0117-1

NO-JET-LAG®

Homeopathic
Jet Lag Prevention

Claims based on traditional homeopathic practice,
not accepted medical evidence.
Not FDA evaluated.

32 TABLETS

SUFFICIENT FOR 50 HOURS OF FLYING